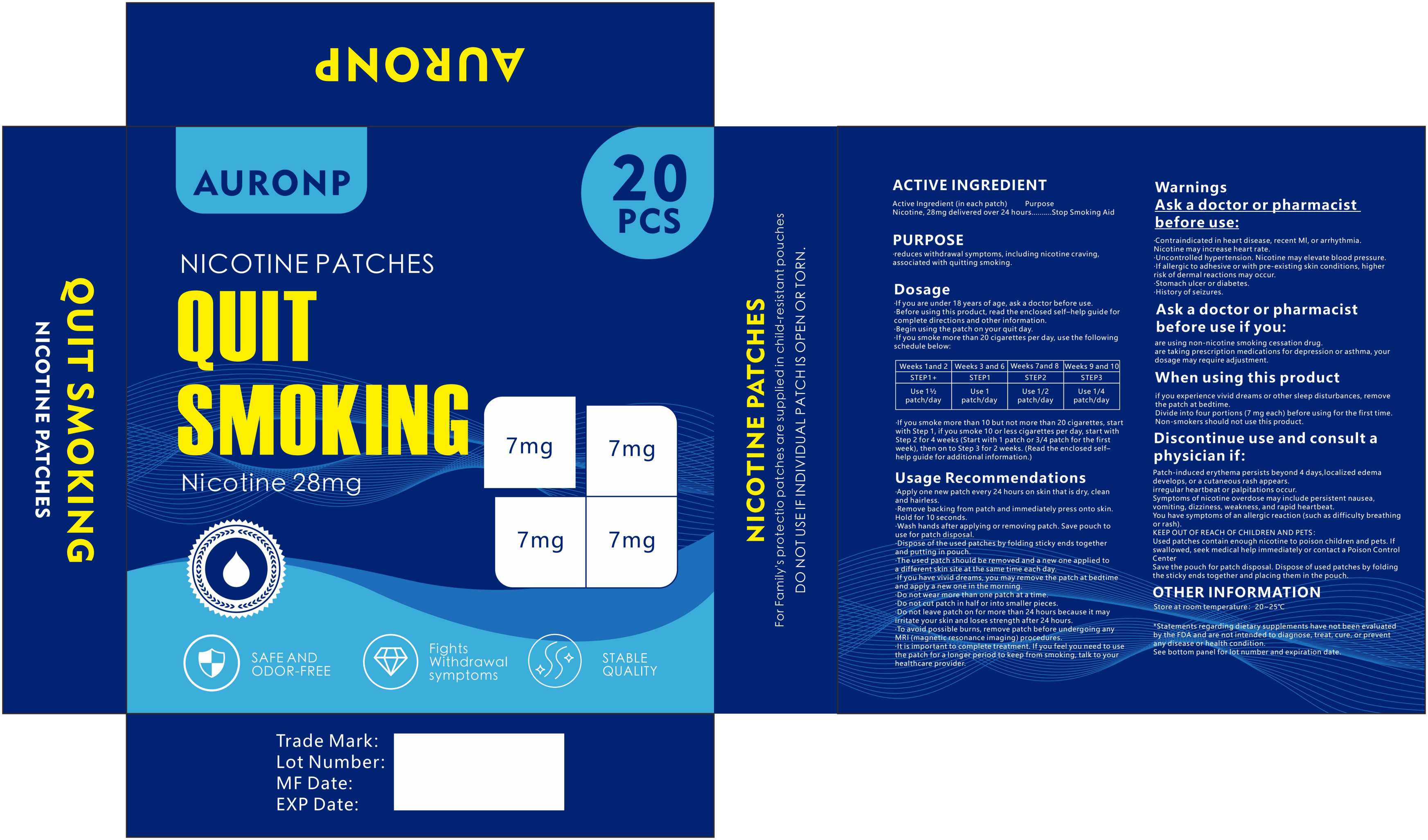 DRUG LABEL: QUIT SMOKING NICOTINE PATCHES
NDC: 84778-087 | Form: PATCH
Manufacturer: Guangzhou Yixin Cross-border E-commerce Co., Ltd.
Category: otc | Type: HUMAN OTC DRUG LABEL
Date: 20250920

ACTIVE INGREDIENTS: NICOTINE 28 mg/100 mg
INACTIVE INGREDIENTS: SILICON DIOXIDE; LACTASE

Active ingredients

Nicotine,28mg delivered over 24 hours.....Stop Smoking Aid

USES

Use reduces withdrawal symptoms,includingnicotine craving, associated withquitting smoking

Purpose

Usereduces withdrawal symptoms,includingassociated withnicotine craving，quitting smoking

WARNINGS

If you are pregnant or breast-feeding, only use thismedicine on the advice of your health care provider.Smoking can seriously harm your child. Try to stopsmoking without using any nicotine replacementmedicine,This medicine is believed to be safer thansmoking.However, the risks to your child from thismedicine are not fully known.

DOSAGE AND ADMINISTRATION SECTION

Heart disease, recent heart attack, or irregualrheartbeat, Nicotine can increase your heart rateHigh blood pressure not controlled withmedication, Nicotine can increase your bloodpressure.An allergy to adhesive tape or have skin problems.because you are more likely to get rashes.Stomach ulcer or diabetes.History of seizures.

DO NOT USE SECTION

Using a non-nicotine stop smoking rugTaking a prescription medicine for depressionor asthma. Your prescription dose may needto be adjusted.

WHEN USING SECTION

Using a non-nicotine stop smoking rugTaking a prescription medicine for depressionor asthma. Your prescription dose may needto be adjusted. to maintain skin health, especially in winter or if you have skin sensitivity.

STOP USE

Stop use and ask a doctor if Feelinguncomfortable or experiencingother sensitive dizziness symptoms

KEEP OUT OF REACH OF CHILDREN.

Keep out of reach of childrenand pets.

INACTIVE INGREDIENT

Colloidal Silicon Dioxide，Lactose，Polyester Film